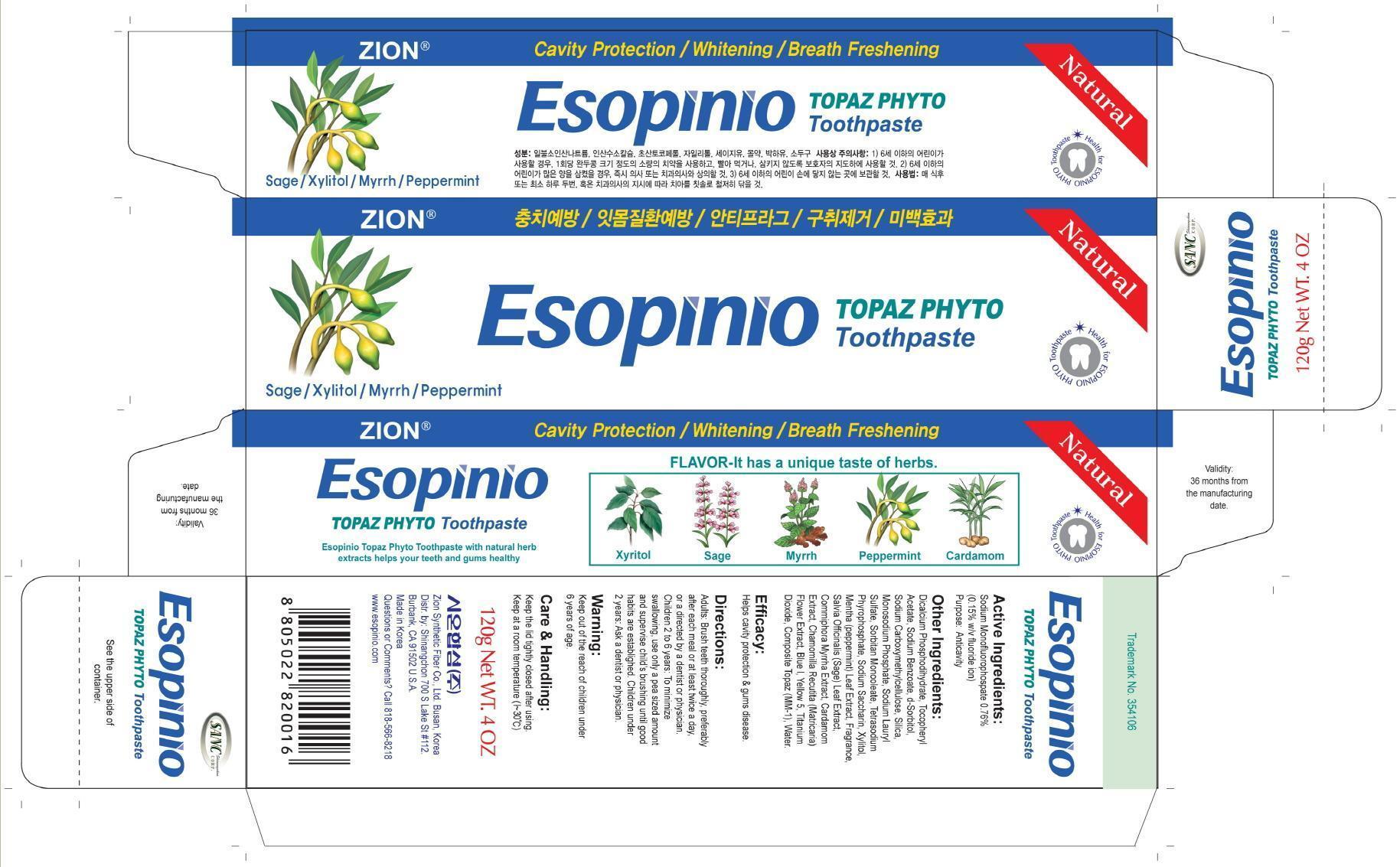 DRUG LABEL: Esopinio Topaz Phyto
NDC: 44781-230 | Form: PASTE, DENTIFRICE
Manufacturer: ZION SYNTHETIC FIBER CO., LTD.
Category: otc | Type: HUMAN OTC DRUG LABEL
Date: 20130816

ACTIVE INGREDIENTS: Sodium Monofluorophosphate 0.91 g/120 g
INACTIVE INGREDIENTS: Sodium Benzoate; Titanium Dioxide; Water

ACTIVE INGREDIENT

Active Ingredient: Sodium Monofluorophosphate 0.76%

INACTIVE INGREDIENT

Inactive Ingredients:
Dicalcium Phosphodihydrate, Tocopheryl Acetate, Sodium Benzoate, d-Sorbitol, Sodium, Carboxymethylcellulose, Silica, Monosodium Phosphate, Sodium Lauryl Sulfate, Sorbitan, Monooleate, Tetrasodium Phyrophosphate, Sodium Saccharin, Xylitol, Mentha (peppermint)
Leaf Extract, Fragrance, Salvia Officinalis (Sage) Leaf Extract, Commiphora Myrrha Extract, Cardamom Extract, Chamomilla Recutita (Matricaria) Flower Extract, Blue l, Yellow 5, Titanium Dioxide, Composite Topaz (MM-1), Water

PURPOSE

1. Cavity Protection
2. Anti-plaque
3. Whitens Teeth
4. Breath Freshening

WARNINGS

If you accidentally swallow more than used for brushing, seek professional help or contact a Poison Control Center iimmediately. Children under 2 years, ask a dentist or physician.

Keep out of reach of children under 6 years of age.

INDICATIONS AND USAGE

1. Brush teeth thoroughly, preferably after each meal, or at least twice a day,
2. Keep the lid tightly closed after using.
3. Keep at a room temperature

DOSAGE AND ADMINISTRATION

1. Children 2 to 6 years of age: To minimize swallowing, use only a pea sized amount and supervise child's brushing until good habits are established.
2. Children under 2 years: Ask your dentist or physician.
3. Adults and children 2 years and older: Brush teeth thoroughly, preferably after each meal, or at least twice a day.